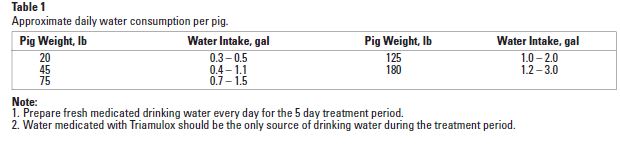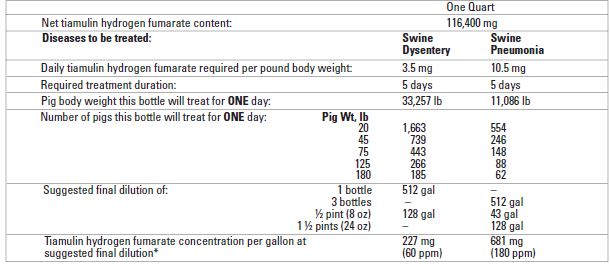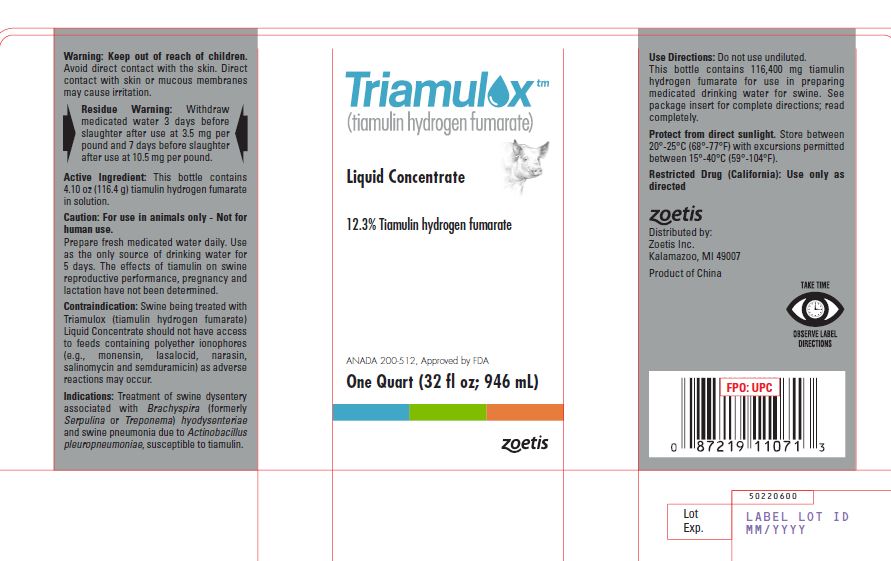 DRUG LABEL: Triamulox
NDC: 54771-8729 | Form: LIQUID
Manufacturer: Zoetis Inc.
Category: animal | Type: OTC ANIMAL DRUG LABEL
Date: 20201012

ACTIVE INGREDIENTS: TIAMULIN FUMARATE 116.4 g/946 mL

TriamuloxLiquid Concentrate

Active ingredient(s)

Active Ingredient

12.3% (116.4g)

Tiamulin hydrogen fumarate

Description

Triamulox (tiamulin hydrogen fumarate) Liquid Concentrate is a solution containing 12.3% tiamulin hydrogen fumarate (w/v) in an aqueous solution. The active ingredient, tiamulin, chemically is 14-desoxy-14-[(2-diethylaminoethyl) mercaptoacetoxy] mutilin hydrogen fumarate, a semi-synthetic diterpene antibiotic. Triamulox is for use only in preparing medicated drinking water for swine.

Actions

Tiamulin is active against Brachyspira (formerly Serpulina or Treponema) hyodysenteriae and Actinobacillus pleuropneumoniae. It is readily absorbed from the gut and can be found in the blood within 30 minutes after dosing.

Indications

Triamulox, when administered in the drinking water for ve consecutive days, is an effective antibiotic for the treatment of swine dysentery associated with Brachyspira (formerly Serpulina or Treponema) hyodysenteriae susceptible to tiamulin at a dose level of 3.5 mg tiamulin hydrogen fumarate per pound of body weight daily and for treatment of swine pneumonia due to Actinobacillus pleuropneumoniae susceptible to tiamulin when given at 10.5 mg tiamulin hydrogen fumarate per pound of body weight daily.

Contraindications: Swine being treated with Triamulox should not have access to feeds containing polyether ionophores (e.g., monensin, lasalocid, narasin, salinomycin and semduramicin) as adverse reactions may occur.

Warnings

Keep out of reach of children. Avoid contact with skin. Direct contact with skin or mucous membranes may cause irritation.

Residue Warning: Withdraw medicated water 3 days before slaughter after treatment at 3.5 mg per pound and 7 days before slaughter following treatment at 10.5 mg per pound body weight.

Caution: For use in drinking water of swine only - Not for use in humans. Prepare fresh medicated water daily. Use as the only source of drinking water for 5 days. The effects of tiamulin on swine reproductive performance, pregnancy and lactation have not been determined.

Adverse Reactions: Overdoses of Triamulox have sometimes produced transitory salivation, vomiting and an apparent calming effect on the pig. If signs of toxicity occur, discontinue use of medicated water and replace with clean, fresh water.

In rare cases, redness of the skin primarily over the ham and underline has been observed during medication. If these signs appear, discontinue use of this drug. Provide ample clean drinking water. Thoroughly rinse (hose down) the housing to remove urine and feces from animal contact surfaces or move the animals to clean pens. If the condition persists, consult your veterinarian.

Studies to evaluate the safety of the water soluble form of tiamulin in breeding swine have not been done.

Use Directions

The concentration of tiamulin in the drinking water must be adjusted to compensate for variation in water consumption due to weight or size of the pig, environmental temperature and other factors. It is important that pigs receive the proper drug dose, 3.5 mg tiamulin hydrogen fumarate per pound for swine dysentery or 10.5 mg tiamulin hydrogen fumarate per pound for swine pneumonia, each day for 5 consecutive days.

Directions for preparing Triamulox Liquid Concentrate medicated solutions: Determine the amount of Triamulox needed to medicate the desired volume of drinking water at the proper concentration. Carefully measure out this amount, add it to the water and stir to thoroughly mix.

Table 2 Triamulox Liquid Concentrate

*Note: Increase or decrease dilution rate as required to obtain proper daily drug dose.

Directions for using Triamulox Liquid Concentrate in medicated proportioners: One quart of Triamulox mixed with water to make four gallons of stock solution and this stock solution metered at one fluid ounce per gallon will provide 227 mg of tiamulin hydrogen fumarate per gallon to 512 gallons of drinking water for treatment of swine dysentery. Three quarts of Triamulox mixed with water to make four gallons of stock solution and this stock solution metered at one -fluid ounce per gallon will provide 681 mg tiamulin hydrogen fumarate per gallon to a total of 512 gallons of drinking water for treatment of swine pneumonia. One pint of Triamulox mixed with water to make two gallons of stock solution and this stock solution metered at one fluid ounce per gallon will provide 227 mg of tiamulin hydrogen fumarate per gallon to 256 gallons of drinking water for treatment of swine dysentery. Use three pints of Triamulox in two gallons of stock solution to be metered at one fluid ounce per gallon to deliver 681 mg per gallon to a total of 256 gallons of drinking water for treatment of swine pneumonia. One-half pint (8 -fluid ounces) of Triamulox diluted with water to make one gallon of stock solution and this stock solution metered at one fluid ounce of drinking water with a medication proportioner will provide 227 mg of tiamulin hydrogen fumarate per gallon to 128 gallons of drinking water for treatment of swine dysentery. Use one and one-half pints of Triamulox per gallon of stock solution to be metered at one fluid ounce per gallon to provide 681 mg per gallon to 128 gallons of drinking water for treatment of swine pneumonia.

In barrels or tanks: Three fluid ounces of Triamulox will medicate 48 gallons of drinking water at 227 mg per gallon for treatment of swine dysentery or 16 gallons at 681 mg per gallon for treatment of swine pneumonia. Measure Triamulox carefully, pour into the proper amount of water and thoroughly mix. The concentration of tiamulin hydrogen fumarate in the stock solution and in the drinking water delivered must be adjusted to compensate for variation in water consumption by pigs due to body weight, environmental and other factors. It is important that the pigs receive the proper drug dose of 3.5 mg of tiamulin hydrogen fumarate per pound of body weight daily for 5 consecutive days for treatment of swine dysentery or a dose of 10.5 mg per pound body weight daily for 5 consecutive days for treatment of swine pneumonia.

Attention: If no response to treatment is obtained within 5 days re-establish the diagnosis. Failure of response may be related to the presence of non-susceptible organisms of other complicating disease conditions. Because of the tendency for the disease to recur on premises with a history of swine dysentery or with swine pneumonia, a control program should be implemented after treatment. Drugs are not substitutes for proper sanitary measures or good management, but should be used in conjunction with such practices.

How Supplied

Container Size

Quart Bottles

(32 fl oz.; 946 ml)

Active Ingredient

12.3% (116.4g)

Tiamulin hydrogen fumarate

Storage

Protect from direct sunlight. Store between 20°-25°C (68°-77°F) with excursions permitted between 15°-40°C (59°-104°F)

other information

Observe expiration date.

Restricted Drug (California): Use only as directed

Approved by FDA under ANADA # 200-512

Manufactured and Distributed by:

Zoetis Inc.

Kalamazoo, MI 49007

Product of China

Revised: August 2020

40031120

Principal Display Panel

Triamulox

(tiamulin hydrogen fumarate)

Liquid Concentrate

12.3% Tiamulin hydrogen fumarate

Approved by FDA under ANADA # 200-512

One Quart (32 oz; 946 mL)